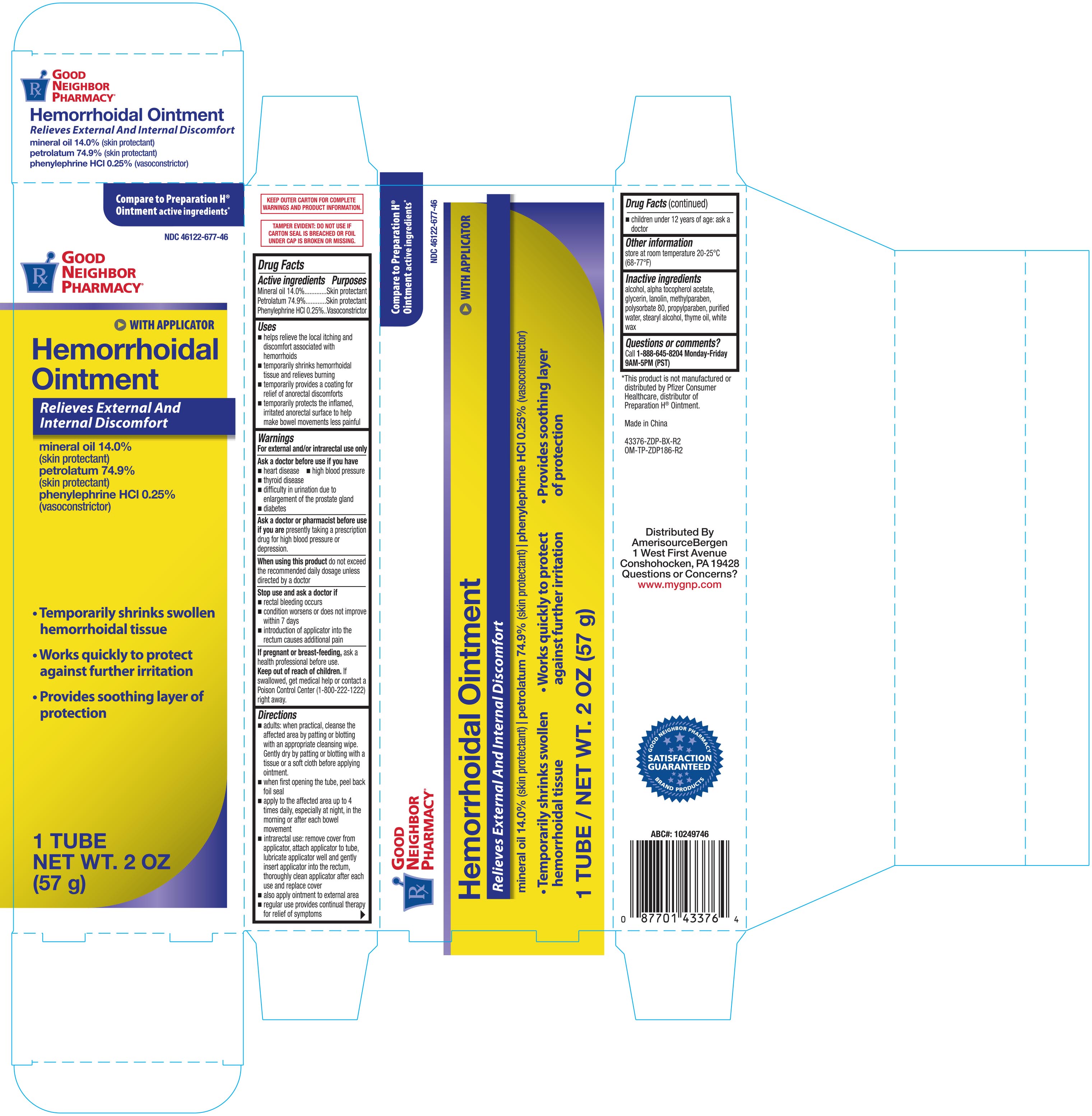 DRUG LABEL: GNP Hemorrhoidal
NDC: 46122-677 | Form: OINTMENT
Manufacturer: Amerisource Bergen
Category: otc | Type: HUMAN OTC DRUG LABEL
Date: 20251030

ACTIVE INGREDIENTS: PHENYLEPHRINE HYDROCHLORIDE 2.5 mg/1 g; PETROLATUM 749 mg/1 g; MINERAL OIL 140 mg/1 g
INACTIVE INGREDIENTS: THYME OIL; WATER; WHITE WAX; .ALPHA.-TOCOPHEROL ACETATE; GLYCERIN; POLYSORBATE 80; PROPYLPARABEN; ALCOHOL; LANOLIN; METHYLPARABEN; STEARYL ALCOHOL

GNP Hemorrhoidal Ointment 2oz (with applicator) 43376 ZDP

Active ingredients Purposes

Mineral oil 14.0%.....................................................Skin protectant

Petrolatum 74.9%....................................................Skin protectant

Phenylephrine HCI 0.25%.......................................Vasconstrictor

Uses

- helps relieve the local itching and discomfort associated with hemorrhoids
- temporarily shrinks hemorrhoidal tissue and relieves burning
- temporarily provides a coating for relief of anorectal discomforts
- temporarily protects the inflamed, irritated anorectal surface to help make bowel movements less painful

Warnings

For external and/or intrarectal use only

Ask a doctor before use if you have

- heart disease
- high blood pressure
- thyroid disease
- difficulty in urination due to enlargement of the prostate gland
- diabetes

Ask a doctor of pharmacist before use if you are presently taking a prescription drug for high blood pressure or depression

When using this product

- do not exceed the recommended daily dosage unless directed by a doctor

Stop use and ask a doctor if

- rectal bleeding occurs
- condition worsens or does not improve within 7 days
- introduction of applicator into rectum causes addition pain

PREGNANCY OR BREAST FEEDING

If pregnant or breast-feeding, ask a health professional before use.

Keep out of reach of children. If swallowed, get medical help or contact a Poison Control Center (1-800-222-1222) right away.

Directions

- adults: when practical, cleanse the affected area by patting or blotting with an appropriate cleansing wipe. Gently dry by patting or blotting with a tissue or a soft cloth before applying ointment.
- when first opening the tube, peel back foil seal
- apply to the affected area up to 4 times daily, especially at night, in the morning or after each bowel movement
- intrarectal use: remove cover from applicator, attach applicator to tube, lubricant applicator well and gently insert applicator into the rectum
- thoroughly cleanse applicator after each use and replace cover
- also apply ointment to external area
- regular use provided continual therapy for relief of symptoms
- children under 12 years of age: ask a doctor

Other information

- store at room temperature 20-25°C (68-77°F)

Inactive ingredients

.alpha.-tocopherol acetate, alcohol, glycerin, lanolin, methyparaben, polysorbate 80, propylparaben, stearyl alcohol, thyme oil, purified water, white wax

DOSAGE AND ADMINISTRATION

Distributed By:

Amerisource Bergen

Made in China